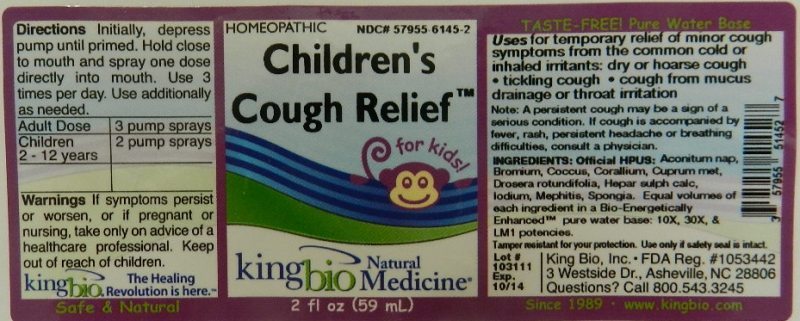 DRUG LABEL: Childrens Cough Relief
NDC: 57955-6145 | Form: LIQUID
Manufacturer: King Bio Inc.
Category: homeopathic | Type: HUMAN OTC DRUG LABEL
Date: 20111201

ACTIVE INGREDIENTS: ACONITUM NAPELLUS 10 [hp_X]/59 mL; BROMINE 10 [hp_X]/59 mL; PROTORTONIA CACTI 10 [hp_X]/59 mL; CORALLIUM RUBRUM EXOSKELETON 10 [hp_X]/59 mL; COPPER 10 [hp_X]/59 mL; DROSERA ROTUNDIFOLIA 10 [hp_X]/59 mL; CALCIUM SULFIDE 10 [hp_X]/59 mL; IODINE 10 [hp_X]/59 mL; MEPHITIS MEPHITIS ANAL GLAND FLUID 10 [hp_X]/59 mL; SPONGIA OFFICINALIS SKELETON, ROASTED 10 [hp_X]/59 mL
INACTIVE INGREDIENTS: WATER

Children's Cough Relief

Active Ingredients

Official HPUS: Aconitum Napellus, Bromium, Coccus Cacti, Corallium Rubrum, Cuprum Metallicum, Drosera Rotundifolia, Hepar Sulphuris Calcareum, Iodium, Mephitis Mephitica and Spongia Tosta.

Reference image cough.jpg

Inactive Ingredient

Equal volumes of each ingredient in a Bio-Energetically Enhanced pure water base: 10X, 30X, and LM1 potencies.

Reference image cough.jpg

Purpose

Uses for temporary relief of minor cough symptoms from the common cold or inhaled irritants: dry or hoarse cough, tickling cough, cough from mucus drainage or throat irritation.

Reference cough.jpg

Dosage and Administration

Direction: Initially, depress pump until primed. Hold close to mouth and spray directly into mouth. Use 3 times per day. Use additionally as needed.
Adult Dose 3 pump sprays
Children (2-12 years) 2 pump sprays
Reference image cough.jpg

Warnings

If symptoms persist or worsen, or if pregnant or nursing, take only on advice of a healthcare professional. Keep out of reach of children.

Tamper resistant for your protection. Use only if safety seal is intact.

Reference image cough.jpg

Keep out of reach of children.

Reference image cough.jpg

Indications and Usage

Uses for temporary relief of minor cough symptoms from the common cold or inhaled irritants:

- dry or hoarse cough
- tickling cough
- cough from mucus drainage or throat irritation

Note: A persistent cough may be a sign of a serious condition. If cough is accompanied by fever, rash, persistent headache or breathing difficulties, consult a physician.
Reference image cough.jpg

PACKAGE LABEL

King Bio, Inc.

3 Westside Drive

Asheville, NC 28806

Questions? Call 800.543.3245